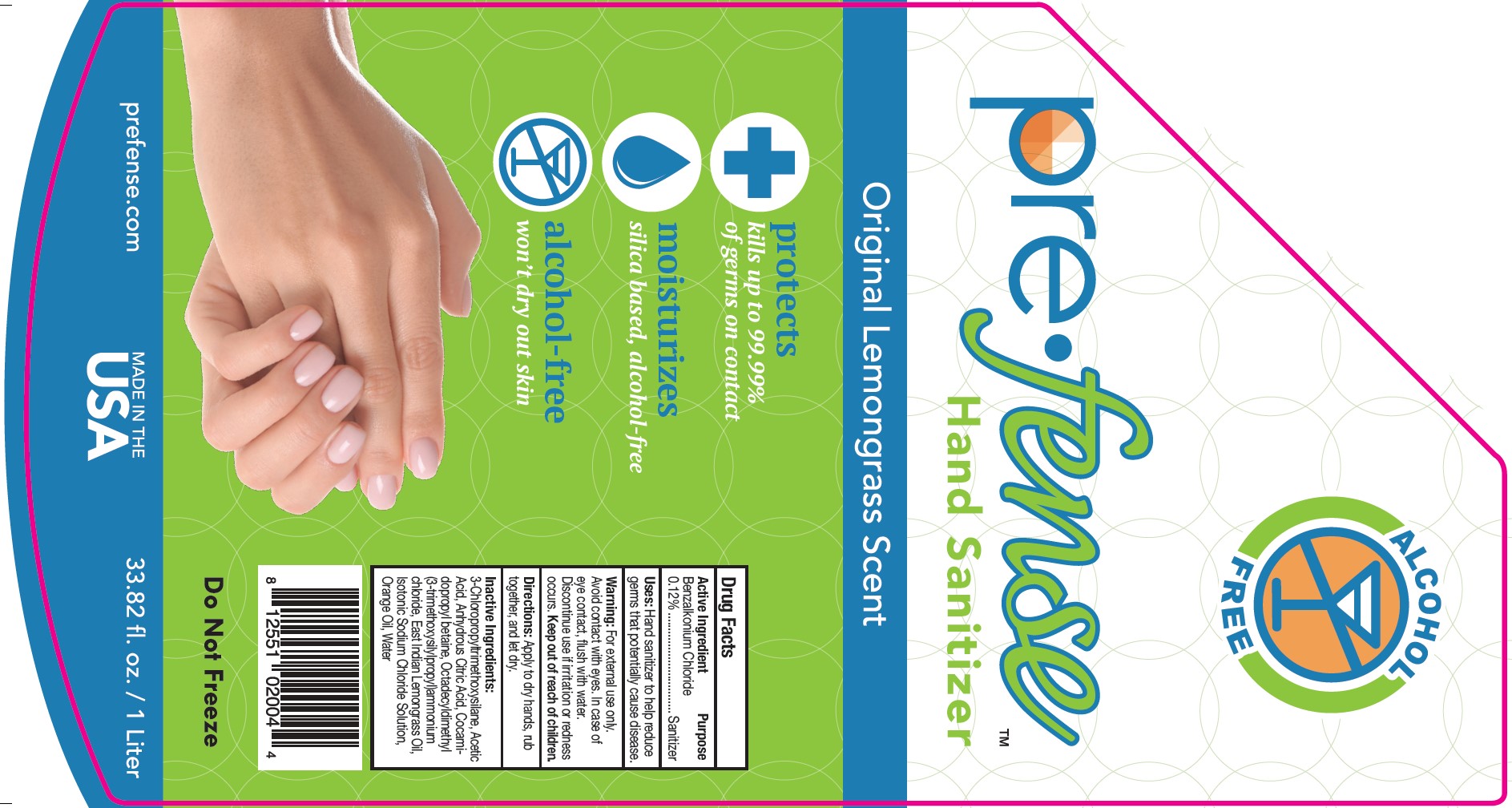 DRUG LABEL: pre fense
NDC: 48404-051 | Form: LIQUID
Manufacturer: Prefense LLC
Category: otc | Type: HUMAN OTC DRUG LABEL
Date: 20251121

ACTIVE INGREDIENTS: BENZALKONIUM CHLORIDE 120 mg/100 mL
INACTIVE INGREDIENTS: ISOTONIC SODIUM CHLORIDE SOLUTION; DIMETHYLOCTADECYL(3-(TRIMETHOXYSILYL)PROPYL)AMMONIUM CHLORIDE; METHYL ALCOHOL; ANHYDROUS CITRIC ACID; WATER; COCAMIDOPROPYL BETAINE; EAST INDIAN LEMONGRASS OIL; ORANGE OIL; (3-CHLOROPROPYL)TRIMETHOXYSILANE

pre•fense Original Lemongrass Scent Hand Sanitizer

Active Ingredient

Drug Facts

Active Ingredient

Benzalkonium Chloride ............0.12%

Purpose

Hand and Skin Sanitizer

Uses:

Hand sanitizer to help reduce germs that potentially cause disease.

Warning:

For external use only. Avoid contact with eyes. In case of eye contact, flush with water. Discontinue use if irritation or redness occurs.

Keep out of reach of children

Directions:

Apply to dry hands, rub together, and let dry.

Inactive Ingredients:

3-Chloropropyltrimethoxysilane, Acetic Acid, Anhydrous Citric Acid, Cocomidoprophyl betaine, Octadecyldimethyl (3-trimethoxysilylpropyl)ammonium chloride, East Indian Lemongrass Oil, Isotonic Sodium Chloride Solution, Orange Oil, Water

RECENT MAJOR CHANGES

Usage statement changed to standard monograph language of "Hand sanitizer to help reduce germs that potentially cause disease."

Directions statement changed to "Apply to dry hands, rub t ogether, and let dry."

Package Label - 1 Liter Pouch

pre•fense™

Hand Sanitizer

Original lemongrass scent

protects

kills up to 99.99% of germs on contact

Moisturizes

silica based, alcohol-free

alcohol-free

won't dry out skin

www.prefense.com

Made in USA

DO NOT FREEZE

33.82 fl. oz./1 Liter